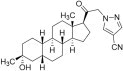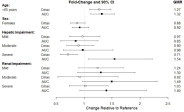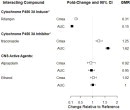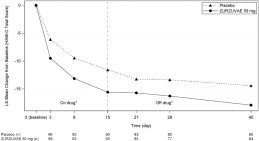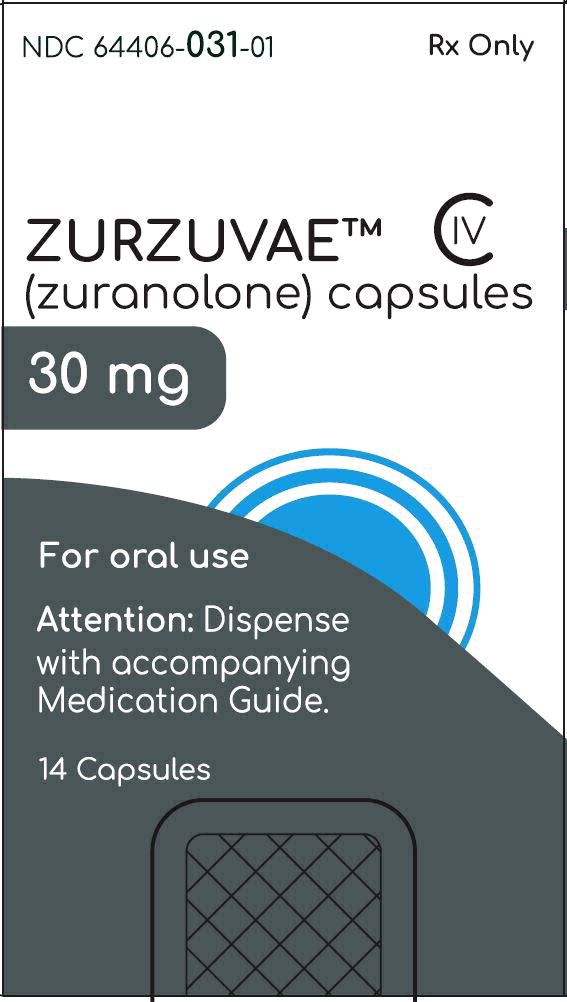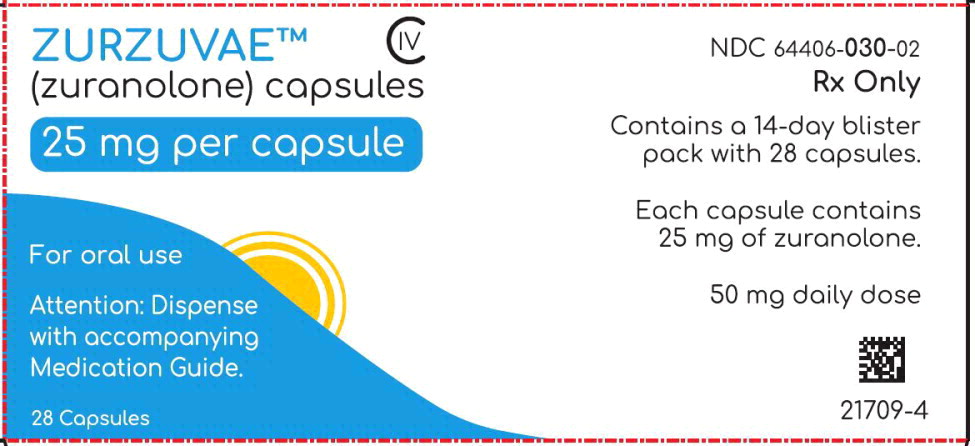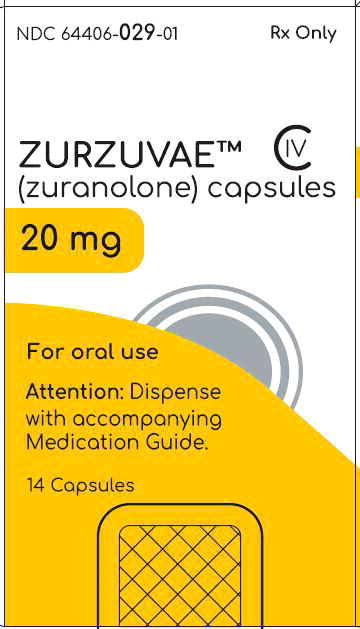 DRUG LABEL: ZURZUVAE
NDC: 64406-031 | Form: CAPSULE
Manufacturer: Biogen MA Inc.
Category: prescription | Type: HUMAN PRESCRIPTION DRUG LABEL
Date: 20241105
DEA Schedule: CIV

ACTIVE INGREDIENTS: ZURANOLONE 30 mg/1 1
INACTIVE INGREDIENTS: SILICIFIED MICROCRYSTALLINE CELLULOSE (125 .MICRO.M, HIGH-DENSITY) 39.28 mg/1 1; MANNITOL 158.85 mg/1 1; CROSCARMELLOSE SODIUM 15.00 mg/1 1; SILICON DIOXIDE 2.500 mg/1 1; SODIUM STEARYL FUMARATE 4.375 mg/1 1

HIGHLIGHTS OF PRESCRIBING INFORMATION

These highlights do not include all the information needed to use ZURZUVAE safely and effectively. See full prescribing information for ZURZUVAE.
ZURZUVAETM (zuranolone) capsules, for oral use, CIV
Initial U.S. Approval: 2023

WARNING: IMPAIRED ABILITY TO DRIVE OR ENGAGE IN OTHER POTENTIALLY HAZARDOUS ACTIVITIES

See full prescribing information for complete boxed warning.

ZURZUVAE causes driving impairment due to central nervous system (CNS) depressant effects. Advise patients not to drive or engage in other potentially hazardous activities until at least 12 hours after administration. Patients may not be able to assess their own driving competence or the degree of impairment caused by ZURZUVAE (5.1, 5.2).

1 INDICATIONS AND USAGE

ZURZUVAE is a neuroactive steroid gamma-aminobutyric acid (GABA) A receptor positive modulator indicated for the treatment of postpartum depression (PPD) in adults. (1)

2 DOSAGE AND ADMINISTRATION

- Administer with fat-containing food. (2.1)
- Recommended dosage is 50 mg orally once daily in the evening for 14 days. (2.1)
- Dosage may be reduced to 40 mg once daily if CNS depressant effects occur. (2.1)
- ZURZUVAE can be used alone or as an adjunct to oral antidepressant therapy. (2.1)
- Severe Hepatic Impairment: Recommended dosage is 30 mg orally once daily in the evening for 14 days. (2.3, 8.6)
- Moderate or Severe Renal Impairment: Recommended dosage is 30 mg orally once daily in the evening for 14 days. (2.4, 8.7)

3 DOSAGE FORMS AND STRENGTHS

Capsules: 20 mg, 25 mg, and 30 mg. (3)

4 CONTRAINDICATIONS

None. (4)

5 WARNINGS AND PRECAUTIONS

- CNS Depressant Effects: ZURZUVAE can cause CNS depressant effects such as somnolence and confusion. If patients develop CNS depression, consider dosage reduction or discontinuation of ZURZUVAE. (5.2)
- Suicidal Thoughts and Behavior: Consider changing the therapeutic regimen, including discontinuing ZURZUVAE, in patients whose PPD worsens, or who experience emergent suicidal thoughts and behaviors. (5.3)
- Embryo-fetal Toxicity: May cause fetal harm. Advise a pregnant woman of the potential risk to an infant exposed to ZURZUVAE in utero. Advise females of reproductive potential of the potential risk to a fetus and to use effective contraception during ZURZUVAE treatment and for one week after the final dose. (5.4, 8.1, 8.2, 8.3)

6 ADVERSE REACTIONS

Most common adverse reactions (incidence ≥5% and greater than placebo) were somnolence, dizziness, diarrhea, fatigue, nasopharyngitis, and urinary tract infection. (6.1)

To report SUSPECTED ADVERSE REACTIONS, contact Biogen at 1-844-987-9882 or FDA at 1-800-FDA-1088 or www.fda.gov/medwatch.

7 DRUG INTERACTIONS

- CNS Depressants: Concomitant use may increase impairment of psychomotor performance or CNS depressant effects. If use with another CNS depressant is unavoidable, consider dosage reduction. (7)
- Strong CYP3A4 Inhibitors: Concomitant use may increase the risk of ZURZUVAE-associated adverse reactions. Reduce the ZURZUVAE dosage to 30 mg orally once daily in the evening for 14 days when used concomitantly with a strong CYP3A4 inhibitor. (2.2, 7)
- CYP3A4 Inducers: Concomitant use may decrease the efficacy of ZURZUVAE. Avoid concomitant use. (2.2, 7)

FULL PRESCRIBING INFORMATION

WARNING: IMPAIRED ABILITY TO DRIVE OR ENGAGE IN OTHER POTENTIALLY HAZARDOUS ACTIVITIES

ZURZUVAE causes driving impairment due to central nervous system (CNS) depressant effects [see Warnings and Precautions (5.1, 5.2)].

Advise patients not to drive or engage in other potentially hazardous activities until at least 12 hours after ZURZUVAE administration for the duration of the 14-day treatment course. Inform patients that they may not be able to assess their own driving competence, or the degree of driving impairment caused by ZURZUVAE [see Warnings and Precautions (5.1)].

1 INDICATIONS AND USAGE

ZURZUVAE is indicated for the treatment of postpartum depression (PPD) in adults.

2 DOSAGE AND ADMINISTRATION

2.1 Recommended Dosage

The recommended dosage of ZURZUVAE is 50 mg taken orally once daily in the evening for 14 days. Administer ZURZUVAE with fat-containing food (e.g., 400 to 1,000 calories, 25% to 50% fat) [see Clinical Pharmacology (12.3)]. If patients experience CNS depressant effects within the 14-day period, consider reducing the dosage to 40 mg once daily in the evening within the 14-day period.

ZURZUVAE can be used alone or as an adjunct to oral antidepressant therapy.

The safety and effectiveness of ZURZUVAE use beyond 14 days in a single treatment course have not been established.

2.2 Dosage Modifications for Concomitant Use with CYP3A4 Inducers or CYP3A4 Inhibitors

CYP3A4 Inducers

Avoid concomitant use of ZURZUVAE with CYP3A4 inducers [see Drug Interactions (7) and Clinical Pharmacology (12.3)].

CYP3A4 Inhibitors

Reduce the ZURZUVAE dosage to 30 mg orally once daily in the evening for 14 days when used concomitantly with a strong CYP3A4 inhibitor [see Drug Interactions (7) and Clinical Pharmacology (12.3)]. No dosage modification is recommended when ZURZUVAE is concomitantly used with a moderate CYP3A4 inhibitor.

2.3 Recommended Dosage in Patients with Hepatic Impairment

The recommended dosage of ZURZUVAE in patients with severe hepatic impairment (Child-Pugh C) is 30 mg orally once daily in the evening for 14 days [see Use in Specific Populations (8.6) and Clinical Pharmacology (12.3)]. The recommended dosage in patients with mild (Child-Pugh A) or moderate (Child-Pugh B) hepatic impairment is the same as those in patients with normal hepatic function.

2.4 Recommended Dosage in Patients with Renal Impairment

The recommended dosage of ZURZUVAE in patients with moderate or severe renal impairment (eGFR <60 mL/min/1.73 m^2) is 30 mg orally once daily in the evening for 14 days [see Use in Specific Populations (8.7) and Clinical Pharmacology (12.3)].

The recommended dosage in patients with mild renal impairment (eGFR 60 to 89 mL/min/1.73 m^2) is the same as those in patients with normal renal function.

2.5 Recommendations Regarding a Missed Dose

If a ZURZUVAE evening dose is missed, take the next dose at the regular time the following evening. Do not take extra capsules on the same day to make up for the missed dose. Continue taking ZURZUVAE once daily until the remainder of the 14-day treatment course is completed.

3 DOSAGE FORMS AND STRENGTHS

Capsules:

- 20 mg: light-orange cap, ivory to light-yellow body, printed with “S-217 20 mg” on body of capsule in black
- 25 mg: light-orange cap, light-orange body, printed with “S-217 25 mg” on body of capsule in black
- 30 mg: orange cap, light-orange body, printed with “S-217 30 mg” on body of capsule in black

4 CONTRAINDICATIONS

None.

5 WARNINGS AND PRECAUTIONS

5.1 Impaired Ability to Drive or Engage in Other Potentially Hazardous Activities

ZURZUVAE causes driving impairment due to central nervous system (CNS) depressant effects [see Warnings and Precautions (5.2)]. In two driving simulation studies, the driving ability of healthy adults was impaired in a dose-dependent manner following repeat nighttime administration of 30 mg of ZURZUVAE (0.6 times the recommended dose) for five days as well as 50 mg of ZURZUVAE (recommended dose) for seven days [see Clinical Studies (14.2)].

Advise patients not to drive a motor vehicle or engage in other potentially hazardous activities requiring complete mental alertness, such as operating machinery, until at least 12 hours after ZURZUVAE administration for the duration of the 14-day treatment course. Inform patients that they may not be able to assess their own driving competence or the degree of driving impairment caused by ZURZUVAE.

5.2 Central Nervous System Depressant Effects

ZURZUVAE can cause CNS depressant effects such as somnolence and confusion.

In Study 1, 36% of patients who received 50 mg of ZURZUVAE and 6% of patients who received placebo daily developed somnolence. In Study 2, 19% of patients who received another zuranolone capsule formulation (approximately equivalent to 40 mg of ZURZUVAE) and 11% of patients who received placebo daily developed somnolence [see Clinical Studies (14)]. In each clinical study, some ZURZUVAE-treated patients developed confusional state. One of these cases was severe, and was also associated with somnolence, dizziness, and gait disturbance. A higher percentage of ZURZUVAE-treated patients, compared to placebo-treated patients, experienced somnolence, dizziness, or confusion that required dosage reduction, interruption, or discontinuation [see Adverse Reactions (6.1)].

Because ZURZUVAE can cause CNS depressant effects, patients may be at higher risk of falls.

Other CNS depressants such as alcohol, benzodiazepines, opioids, tricyclic antidepressants, or drugs that increase zuranolone concentration, may increase impairment of psychomotor performance or CNS depressant effects such as somnolence, cognitive impairment, and the risk of respiratory depression in ZURZUVAE-treated patients [see Drug Interactions (7)].

To reduce the risk of CNS depressant effects and/or mitigate CNS depressant effects that occurs with ZURZUVAE treatment:

- If patients develop CNS depressant effects, consider dosage reduction or discontinuation of ZURZUVAE [see Dosage and Administration (2.1)].
- If use with another CNS depressant is unavoidable, consider dosage reduction.
- Reduce the ZURZUVAE dosage in patients taking strong CYP3A4 inhibitors [see Dosage and Administration (2.2)].

5.3 Suicidal Thoughts and Behavior

In pooled analyses of placebo-controlled trials of chronically administered antidepressant drugs (SSRIs and other antidepressant classes) that included approximately 77,000 adult patients and 4,500 pediatric patients, the incidence of suicidal thoughts and behaviors in antidepressant-treated patients age 24 years and younger was greater than in placebo-treated patients. There was considerable variation in risk of suicidal thoughts and behaviors among drugs, but there was an increased risk identified in young patients for most drugs studied. There were differences in absolute risk of suicidal thoughts and behaviors across the different indications, with the highest incidence in patients with major depressive disorder (MDD). The drug-placebo differences in the number of cases of suicidal thoughts and behaviors per 1000 patients treated are provided in Table 1.

Table 1 Risk Differences of the Number of Patients with Suicidal Thoughts or Behaviors in the Pooled Placebo-Controlled Trials of Antidepressants in Pediatric* and Adult Patients
Age Range (years) | Drug-Placebo Difference in Number of Patients with Suicidal Thoughts or Behaviors per 1000 Patients Treated
 | Increases Compared to Placebo
<18 | 14 additional patients
18-24 | 5 additional patients
 | Decreases Compared to Placebo
25-64 | 1 fewer patient
*ZURZUVAE is not approved in pediatric patients.

ZURZUVAE does not directly affect monoaminergic systems. Consider changing the therapeutic regimen, including discontinuing ZURZUVAE, in patients whose depression becomes worse or who experience emergent suicidal thoughts and behaviors.

5.4 Embryo-fetal Toxicity

Based on findings from animal studies, ZURZUVAE may cause fetal harm when administered to a pregnant woman. In rat studies following exposure during gestation or throughout gestation and lactation, adverse effects on development (fetal malformations, embryofetal and offspring mortality, growth deficits) were observed. In addition, neuronal death was observed in rats exposed to zuranolone during a period of brain development that in humans begins during the third trimester of pregnancy and continues during the first few years after birth [see Use in Specific Populations (8.1, 8.2)].

Advise a pregnant woman of the potential risk to an infant exposed to ZURZUVAE in utero. Advise females of reproductive potential to use effective contraception during treatment with ZURZUVAE and for one week after the final dose [see Use in Specific Populations (8.1, 8.3)].

6 ADVERSE REACTIONS

The following adverse reactions are discussed in more detail in other sections of the labeling:

- Impaired Ability to Drive or Engage in Other Potentially Hazardous Activities [see Warnings and Precautions (5.1)]
- Central Nervous System Depressant Effects [see Warnings and Precautions (5.2)]
- Suicidal Thoughts and Behavior [see Warnings and Precautions (5.3)]

6.1 Clinical Trial Experience

Because clinical trials are conducted under widely varying conditions, adverse reaction rates observed in the clinical trials of a drug cannot be directly compared to rates in the clinical trials of another drug and may not reflect the rates observed in practice.

The safety of ZURZUVAE for the treatment of postpartum depression (PPD) was evaluated in two placebo-controlled clinical studies in 347 women with PPD treated with 50 mg of ZURZUVAE (Study 1), or with another zuranolone capsule formulation approximately equivalent to 40 mg of ZURZUVAE (Study 2) once daily for 14 days [Clinical Studies (14.1)]. The studies included adult patients age 18 to 44 years diagnosed with PPD.

Across PPD clinical studies at all doses studied (Studies 1 and 2), serious adverse reactions included confusional state (1%) [Clinical Studies (14.1)].

In Study 1, the incidence of adverse reactions that led to discontinuation in patients treated with 50 mg of ZURZUVAE and placebo was 2% and 1%, respectively. The most common adverse reaction leading to treatment discontinuation in ZURZUVAE-treated patients was somnolence.

Dosage reduction due to an adverse reaction occurred in 14% of ZURZUVAE-treated patients. The most common adverse reactions leading to dosage reduction in ZURZUVAE-treated patients were somnolence (10%) and dizziness (6%).

The most common adverse reactions (≥5% and greater than placebo) in ZURZUVAE-treated patients were somnolence, dizziness, diarrhea, fatigue, and urinary tract infection.

Table 2 summarizes the adverse reactions that occurred in ≥2% of patients with PPD treated with 50 mg of ZURZUVAE and at a higher incidence than in patients who received placebo in Study 1.

Table 2 Adverse Reactions that Occurred in ≥2% of Patients with PPD Treated with 50 mg of ZURZUVAE and Greater than in Patients Treated with Placebo (Study 1)
Adverse Reaction | Placebo (N=98) (%) | 50 mg of ZURZUVAE (N=98) (%)
Somnolence^1 | 6 | 36
Dizziness^2 | 9 | 13
Diarrhea | 2 | 6
Fatigue^3 | 2 | 5
Urinary tract infection | 4 | 5
Memory impairment | 0 | 3
Abdominal pain^4 | 0 | 3
Tremor | 0 | 2
Hypoesthesia | 0 | 2
Muscle twitching | 0 | 2
Myalgia | 0 | 2
COVID-19 | 0 | 2
Anxiety | 1 | 2
Rash | 1 | 2
^1 Somnolence includes sedation and hypersomnia
^2 Dizziness includes vertigo
^3 Fatigue includes asthenia
^4 Abdominal pain includes upper abdominal pain

In Study 2, the incidence of adverse reactions that led to discontinuation in patients who received another zuranolone capsule formulation (approximately equivalent to 40 mg of ZURZUVAE) and placebo was 1% and 0%, respectively. The adverse reaction that led to treatment discontinuation was somnolence.

Dosage reduction due to an adverse reaction occurred in 4% of zuranolone-treated patients. The adverse reactions that led to dosage reduction were somnolence and confusional state.

The most common (≥5% and greater than placebo) adverse reactions in zuranolone-treated patients were somnolence, nasopharyngitis, dizziness, fatigue, and diarrhea.

Table 3 summarizes the adverse reactions that occurred in ≥2% of zuranolone-treated patients with PPD and at a higher incidence than in placebo-treated patients in Study 2.

Table 3 Adverse Reactions that Occurred in ≥2% of Patients with PPD Treated with Another Zuranolone Capsule Formulation* and Greater than in Patients Treated with Placebo (Study 2)
Adverse Reaction | Placebo (N=73) (%) | Another Zuranolone Capsule Formulation* (N=78) (%)
Somnolence^1 | 11 | 19
Nasopharyngitis^2 | 3 | 9
Dizziness | 6 | 8
Fatigue^3 | 1 | 5
Diarrhea | 3 | 5
Dry mouth | 0 | 4
Sinus congestion | 0 | 3
Toothache | 0 | 3
^1 Somnolence includes sedation
^2 Nasopharyngitis includes upper respiratory tract infection
^3 Fatigue includes lethargy
* This capsule formulation of zuranolone is approximately equivalent to 40 mg of ZURZUVAE.

7 DRUG INTERACTIONS

Table 4 displays clinically important drug interactions with ZURZUVAE.

Table 4 Clinically Important Drug Interactions with ZURZUVAE
CNS Depressant Drugs and Alcohol
Clinical Impact | Due to additive pharmacological effects, the concomitant use of CNS depressant drugs, including alcohol, may increase impairment of psychomotor performance or CNS depressant effects.
Management | If use with another CNS depressant is unavoidable, consider dosage reduction. Caution should be used when ZURZUVAE is administered in combination with other CNS drugs or alcohol [see Warnings and Precautions (5.2)].
Strong CYP3A4 Inhibitors
Clinical Impact | Concomitant use of ZURZUVAE with a strong CYP3A4 inhibitor increases the exposure of zuranolone [see Clinical Pharmacology (12.3)], which may increase the risk of ZURZUVAE-associated adverse reactions.
Management | Reduce the ZURZUVAE dosage when used with a strong CYP3A4 inhibitor [see Dosage and Administration (2.3)].
CYP3A4 Inducers
Clinical Impact | Concomitant use of ZURZUVAE with a CYP3A4 inducer decreases the exposure of zuranolone [see Clinical Pharmacology (12.3)], which may reduce the efficacy of ZURZUVAE.
Management | Avoid concomitant use of ZURZUVAE with CYP3A4 inducers [see Dosage and Administration (2.3)].

8 USE IN SPECIFIC POPULATIONS

8.1 Pregnancy

Pregnancy Exposure Registry

There is a pregnancy exposure registry that monitors pregnancy outcomes in women exposed to antidepressants, including ZURZUVAE, during pregnancy. Healthcare providers are encouraged to register patients by calling the National Pregnancy Registry for Antidepressants at 1-844-405-6185 or visiting online at https://womensmentalhealth.org/research/pregnancyregistry/antidepressants/

Risk Summary

Based on findings from animal studies, ZURZUVAE may cause fetal harm. Advise pregnant women of the potential risk to a fetus. Available data on ZURZUVAE use in pregnant women from the clinical development program are insufficient to evaluate for a drug-associated risk of major birth defects, miscarriage, or adverse maternal or fetal outcomes.

In animals, oral administration of zuranolone to pregnant rats during organogenesis resulted in developmental toxicity, including embryofetal death and fetal malformations, with a no adverse effect level (NOAEL) associated with maternal plasma exposures 7 times greater than in humans at the maximum recommended human dose (MRHD) of 50 mg. Oral administration of zuranolone to rats during pregnancy and lactation resulted in developmental toxicity in the offspring, including, perinatal mortality, at maternal exposures similar to that in humans at the MRHD. Developmental toxicity was observed at doses that were also maternally toxic. Neuronal death was observed in rats exposed to zuranolone during a period of brain development that begins during the third trimester of pregnancy in humans and continues up to a few years after birth.

The estimated background risk of major birth defects and miscarriage for the indicated population is unknown. All pregnancies have a background risk of birth defect, loss, or other adverse outcomes. In the U.S. general population, the estimated background risk of major birth defects and miscarriage in clinically recognized pregnancies is 2% to 4% and 15% to 20%, respectively.

Data

Animal Data

Oral administration of zuranolone (0, 2.5, 7.5, or 22.5 mg/kg/day) to pregnant rats during organogenesis resulted in increased incidences of fetal malformations, reductions in embryofetal survival, and reduced fetal body weights as well as maternal mortality and sedation at the highest dose. The no effect dose (7.5 mg/kg/day) for adverse effects on embryofetal development was associated with maternal exposures (AUC) approximately 7 times that in humans at the MRHD of 50 mg.

Potential adverse effects of zuranolone on embryofetal development in pregnant rabbits were not adequately assessed.

Oral administration of zuranolone (0, 1, 4, or 10 mg/kg/day) to rats throughout pregnancy and into lactation resulted in increased perinatal mortality and persistent bodyweight reductions in the offspring at the mid and high doses, which also produced maternal mortality and adverse clinical signs. The no-effect dose (1 mg/kg/day) for adverse effects on pre- and postnatal development in rats was associated with maternal exposures (AUC) approximately 2 times that in the humans at the MRHD.

Oral administration of a single dose of zuranolone (0, 2.5, or 7.5 mg/kg) to rats on postnatal day 7 resulted in increased apoptotic neurodegeneration in the brain at the highest dose tested. The no-effect dose (2.5 mg/kg) was associated with plasma exposures (AUC) comparable to that in humans at the MRHD. Brain development on PND 7 in rats corresponds to a period of brain development that begins during the third trimester of pregnancy in humans and continue up to a few years after birth.

8.2 Lactation

Risk Summary

Available data from a clinical lactation study in 14 women indicate that zuranolone is present in low levels in human milk (see Data). There are no data on the effects of zuranolone on a breastfed infant and limited data on the effects on milk production.

The developmental and health benefits of breastfeeding should be considered along with the mother's clinical need for ZURZUVAE and any potential adverse effects on the breastfed child from ZURZUVAE or from the underlying maternal condition.

Data

A steady-state milk study was conducted in 14 healthy lactating women treated with daily oral administration of 30 mg of ZURZUVAE for 5 days. At steady state (Day 5), the calculated maximum relative infant dose for ZURZUVAE was < 1%. The daily infant dose was low (approximately 0.0013 mg/kg/day), reflecting a mean relative infant dose of 0.357% compared to the maternal dose. Concentrations of ZURZUVAE in breastmilk were below the level of quantification limit (BQL) by 4-6 days after the last dose.

8.3 Females and Males of Reproductive Potential

Based on animal studies, ZURZUVAE may cause embryo-fetal harm when administered to a pregnant woman [see Warnings and Precautions (5.4) and Use in Specific Populations (8.1)].

Contraception

Advise female patients of reproductive potential to use effective contraception during treatment with ZURZUVAE and for one week after the final dose.

8.4 Pediatric Use

The safety and effectiveness of ZURZUVAE in pediatric patients have not been established.

8.5 Geriatric Use

PPD is a condition associated with pregnancy; there is no geriatric experience with ZURZUVAE in patients with PPD.

8.6 Hepatic Impairment

Exposure to zuranolone was increased in patients with severe hepatic impairment. The recommended ZURZUVAE dosage in patients with severe hepatic impairment (Child-Pugh C) is lower than patients with normal hepatic function [see Dosage and Administration (2.3) and Clinical Pharmacology (12.3)].

The recommended ZURZUVAE dosage in patients with mild or moderate hepatic impairment (Child-Pugh A or Child-Pugh B) is the same as those with normal hepatic function [see Clinical Pharmacology (12.3)].

8.7 Renal Impairment

Exposure to zuranolone was increased in patients with moderate (eGFR 30 to 59 mL/min/1.73 m^2) and severe (eGFR 15 to 29 mL/min/1.73 m^2) renal impairment [see Clinical Pharmacology (12.3)].

The recommended ZURZUVAE dosage in patients with moderate and severe renal impairment is lower than those with normal renal function [see Dosage and Administration (2.4)]. The recommended dosage in patients with mild renal impairment (eGFR 60 to 89 mL/min/1.73 m^2) is the same as those in patients with normal renal function. ZURZUVAE has not been studied in patients with eGFR of < 15 mL/min/1.73 m^2 or patients requiring dialysis.

9 DRUG ABUSE AND DEPENDENCE

9.1 Controlled Substance

ZURZUVAE contains zuranolone, a Schedule IV controlled substance.

9.2 Abuse

Zuranolone has abuse potential with associated risks of misuse, abuse, and substance use disorder including addiction. Abuse is the intentional non-therapeutic use of a drug, even once, for its desired psychological or physiological effects. Misuse is the intentional use, for therapeutic purposes, of a drug by an individual in a way other than prescribed by a health care provider or for whom it was not prescribed. Drug addiction is a cluster of behavioral, cognitive, and physiological phenomena that may include a strong desire to take the drug, difficulties in controlling drug use (e.g., continuing drug use despite harmful consequences, giving a higher priority to drug use than other activities and obligations), and possible tolerance or physical dependence. Individuals with a history of drug abuse or substance use disorders may be at a greater risk of these outcomes with ZURZUVAE.

In a human abuse potential study, single oral doses of 30 mg, 60 mg, and 90 mg of ZURZUVAE (0.6 times, 1.2 times, and 1.8 times the recommended daily dose, respectively) were compared to single oral doses of alprazolam (1.5 mg and 3 mg) and placebo in healthy, nondependent individuals with a history of recreational CNS depressant use. The study demonstrated that ZURZUVAE has dose-dependent abuse potential comparable to alprazolam and greater abuse potential than placebo on positive subjective measures of “drug liking,” “overall drug liking,” “take drug again,” “high,” and “good drug effects.” In the human abuse potential study, dose-dependent, abuse-related adverse reactions, including euphoric mood, feeling drunk, and somnolence, were reported with ZURZUVAE use.

9.3 Dependence

ZURZUVAE may produce physical dependence. Physical dependence is a state that develops as a result of physiological adaptation in response to repeated drug use, manifested by withdrawal signs and symptoms after abrupt discontinuation or a significant dose reduction of a drug.

Adverse reactions reported upon discontinuation of zuranolone in healthy subjects who received 50 mg of zuranolone for 5 to 7 days (on the 7th day subjects received 50 mg or 100 mg) included: insomnia, palpitations, decreased appetite, nightmare, nausea, hyperhidrosis, and paranoia. These adverse reactions indicate a potential for physical dependence with zuranolone. These adverse reactions were mild-to-moderate in severity.

The risk for developing physical dependence and a subsequent withdrawal syndrome upon abrupt ZURZUVAE discontinuation for individuals who take a higher than recommended dosage and/or use ZURZUVAE for a longer duration than recommended [see Dosage and Administration (2.1)] has not been evaluated in clinical studies. However, convulsions were observed in a dog upon abrupt zuranolone discontinuation after dogs were administered zuranolone for 14 days at doses that produced exposures higher than the maximum recommended human dose [see Nonclinical Toxicology (13.2)].

10 OVERDOSAGE

There was a case of intentional overdose with ZURZUVAE reported during premarketing clinical trials. The patient took 330 mg (6.5 times the maximum recommended dose) of ZURZUVAE and was reported to be in an altered state of consciousness. The event resolved the next day, following treatment with intravenous fluids.

Overdosage with ZURZUVAE may result in excessive CNS depressant effects such as somnolence and disturbance in consciousness. There is no specific antidote for ZURZUVAE overdosage.

Consider contacting the Poison Help Line (1-800-222-1222) or a medical toxicologist for additional overdosage management recommendations.

11 DESCRIPTION

ZURZUVAE contains zuranolone, a neuroactive steroid gamma-aminobutyric acid (GABA) A receptor positive modulator. The chemical name is 1-[(3α, 5β)-3-hydroxy-3-methyl-20- oxo-19-norpregnan-21-yl]-1H-pyrazole-4-carbonitrile and it has the following chemical structure:

The molecular formula of zuranolone is C25H35N3O2 and the relative molecular mass is 409.57.

Zuranolone is a white to off-white, non-hygroscopic, crystalline solid. It is sparingly soluble in ethyl acetate, methanol, and ethanol; slightly soluble in methyl tert-butyl ether and isopropanol; soluble in tetrahydrofuran and acetone; and practically insoluble in water and n-heptane.

ZURZUVAE is available in 20 mg, 25 mg, and 30 mg capsules for oral administration. Each capsule contains zuranolone as the active ingredient and the following inactive ingredients: colloidal silicon dioxide, croscarmellose sodium, mannitol, microcrystalline cellulose, and sodium stearyl fumarate. The capsule shells contain gelatin, red iron oxide, titanium dioxide, and yellow iron oxide, and are imprinted with black ink (containing ammonium hydroxide, black iron oxide, propylene glycol, and shellac glaze).

12 CLINICAL PHARMACOLOGY

12.1 Mechanism of Action

The mechanism of action of zuranolone in the treatment of PPD is not fully understood, but is thought to be related to its positive allosteric modulation of GABAA receptors.

12.2 Pharmacodynamics

Cardiac Electrophysiology

At two times the maximum recommended dose, ZURZUVAE does not cause clinically significant QTc interval prolongation.

Psychomotor Performance with Alcohol or Alprazolam

Co-administration of repeated 50 mg daily doses of ZURZUVAE with alcohol or alprazolam led to impairment in psychomotor performance [see Warnings and Precautions (5.2), Drug Interactions (7)].

12.3 Pharmacokinetics

Zuranolone exposure (Cmax and AUC) increased approximately dose proportionally with doses ranging from 30 mg to 60 mg (1.2 times of the recommended dosage of ZURZUVAE) with a moderate-fat meal (700 calories; 30% fat). Once-daily administration of ZURZUVAE resulted in accumulation of approximately 1.5-fold in systemic exposures and steady state was achieved in 3 to 5 days.

Absorption

Following oral administration, peak zuranolone concentrations occur at 5 to 6 hours (Tmax).

The absolute bioavailability of ZURZUVAE was not evaluated.

Effect of Food

Following administration of 30 mg of ZURZUVAE to healthy subjects, the Cmax increased by approximately 3.5-fold and the AUClast increased by approximately 1.8-fold with a low-fat meal (400 to 500 calories, 25% fat) compared to fasted conditions. The Cmax increased by approximately 4.3-fold and the AUClast increased by approximately 2-fold with a high-fat meal (800 to 1,000 calories, 50% fat) compared to fasted conditions. The Tmax was not impacted by food.

Distribution

The volume of distribution of zuranolone following oral administration is greater than 500 L. The mean blood-to-plasma concentration ratio ranged from 0.54 to 0.58. Plasma protein binding is greater than 99.5%.

Elimination

The terminal half-life of zuranolone is approximately 19.7 to 24.6 hours in an adult population. The mean apparent clearance (CL/F) of zuranolone is 33 L/h.

Metabolism

Zuranolone undergoes extensive metabolism, with CYP3A4 identified as a primary enzyme involved. There were no circulating human metabolites greater than 10% of total drug-related materials and none are considered to contribute to the therapeutic effects of zuranolone.

Excretion

Following oral administration of radiolabeled zuranolone, 45% of the dose was recovered in urine as metabolites with negligible unchanged zuranolone and 41% in feces as metabolites with less than 2% as unchanged zuranolone.

Specific Populations

Racial Groups

Black or African American participants had a 14% higher CL/F compared to participants of other races (Asian, White, or other).

Male and Female Patients, Patients with Renal Impairment, Patients with Hepatic Impairment

Exposures of zuranolone in specific populations are summarized in Figure 1 [see Dosage and Administration (2.4, 2.5) and Use in Specific Populations (8.6, 8.7)].

Figure 1 Effect of Specific Populations on the Pharmacokinetics of Zuranolone

Data shown for participants ≥65 years relative to younger participants (18 to 45 years); female participants relative to male participants; renal and hepatic impairment relative to participants with normal renal and hepatic function, respectively. Hepatic impairment: Mild (Child-Pugh Class A); moderate (Child-Pugh Class B); severe (Child-Pugh Class C). Renal impairment: Mild (eGFR 60-89 mL/min/1.73m^2); moderate (eGFR 30-59 mL/min/1.73m^2); severe (eGFR <30 mL/min/1.73m^2 and not on dialysis). CI = confidence interval; GMR = geometric mean ratio

Drug Interaction Studies

The effect of co-administered drugs on the pharmacokinetics of zuranolone is summarized in Figure 2 [see Dosage and Administration (2.3) and Drug Interactions (7)].

Figure 2 Effect of Co-Administered Drugs on the Pharmacokinetics of Zuranolone

Data shown are zuranolone plus co-administered drug relative to zuranolone alone. CI = confidence interval; GMR = geometric mean ratio; * clinically significant drug interaction

ZURZUVAE did not affect the pharmacokinetics of alprazolam or ethanol. Increased impairment of psychomotor performance was observed when ZURZUVAE was co-administered with alprazolam or ethanol [see Warnings and Precautions (5.2) and Drug Interactions (7)].

In Vitro Studies

Enzyme systems: Zuranolone is not an inhibitor of CYP1A2, 2B6, 2C19, 2C8, 2C9, 2D6 or 3A4. Zuranolone is not an inducer for CYP1A2, CYP2B6 or CYP3A4 at the therapeutic dose range.

Transporter systems: Zuranolone is not a substrate of P-glycoprotein (P-gp), BCRP, OATP1B1 or OATP1B3. Zuranolone does not inhibit P-gp, BCRP, BSEP, OATP1B1, OATP1B3, OAT1, OAT2, OCT1, OCT2, MATE1, or MATE2.

13 NONCLINICAL TOXICOLOGY

13.1 Carcinogenesis, Mutagenesis, Impairment of Fertility

Carcinogenesis

Oral administration of zuranolone in a 26-week carcinogenicity study in transgenic mice (0, 10, 30, or 100 mg/kg/day), and in a 104-week carcinogenicty study in rats (0, 2, 6, or 20 mg/kg/day in males and 0, 0.2, 0.6, or 1.5 mg/kg/day in females) was not associated with increases in tumors in either species. Plasma exposures (AUC) in rats at the highest dose tested were approximately 4 times that in humans at the maximum recommended human dose (MRHD) of 50 mg.

Mutagenesis

Zuranolone was not genotoxic when tested in an in vitro microbial mutagenicity (Ames) assay, an in vitro chromosome aberration assay in Chinese hamster ovary cells, and an in vivo bone marrow micronucleus assay in rats.

Impairment of Fertility

Oral administration of zuranolone (0, 3, 10, or 30 mg/kg/day) to male rats prior to and during mating with untreated females resulted in increased post-implantation loss and a corresponding decrease in the number of viable embryos at the high dose, which was also paternally toxic. There were no adverse effects on fertility or sperm parameters. Adverse effects on reproduction were not observed when males were remated after a 6-week treatment-free period. The no effect dose (10 mg/kg/day) for male reproductive toxicity was associated with a plasma zuranolone exposure (AUC) of approximately 4 times the human exposure at the MRHD. Oral administration of zuranolone (0, 1, 3, or 10 mg/kg/day) to female rats prior to and throughout mating and continuing through early gestation resulted in disruption of estrous cyclicity at the high dose, but there were no adverse effects on fertility or early embryonic development. The no-effect dose (3 mg/kg/day) for female reproductive toxicity was associated with exposures approximately 4 times that in humans at the MRHD.

13.2 Animal Toxicology and/or Pharmacology

Death was observed in 1 dog four days after repeat dosing with 2.5 mg/kg for 9 months was stopped. Death/euthanasia in 2 dogs was also observed 2 to 4 days after dosing with 2.5 mg/kg for 14 days was stopped. Convulsions were observed in 1 dog three days after repeat dosing with 2.5 mg/kg for 14 days was stopped. Plasma exposure (AUC) at the no-effect dose in dogs was approximately 3 times the human exposure at the MRHD.

14 CLINICAL STUDIES

14.1 Postpartum Depression

The efficacy of ZURZUVAE for the treatment of postpartum depression (PPD) in adults was demonstrated in two randomized, placebo-controlled, double-blind, multicenter studies (Study 1, NCT04442503 and Study 2, NCT02978326) in women with PPD who met the Diagnostic and Statistical Manual of Mental Disorders criteria for a major depressive episode (DSM-5) with onset of symptoms in the third trimester or within 4 weeks of delivery. In these studies, concomitant use of existing oral antidepressants was allowed for patients taking a stable dose of oral antidepressant for at least 30 days before baseline. These studies included patients with HAMD-17 scores ≥ 26 at baseline.

In Study 1, patients received 50 mg of ZURZUVAE (N=98) or placebo (N=97) once daily in the evening with fat-containing food for 14 days, with the option to reduce the dosage based on tolerability to 40 mg once daily of ZURZUVAE or placebo. The patients were followed for a minimum of 4 weeks after the 14-day treatment course.

In Study 2, patients received another zuranolone capsule formulation (approximately equivalent to 40 mg of ZURZUVAE) (N=76) or placebo (N=74) once daily in the evening with food for 14 days. The patients were followed for a minimum of 4 weeks after the 14-day treatment course.

Baseline Demographics and Disease Characteristics

In Studies 1 and 2, the baseline demographic and disease characteristics of patients were similar between the ZURZUVAE and placebo groups. In Study 1, patients had a mean age of 30 years (range 19 to 44 years); were 70% White, 22% Black or African American, 1% Asian, and 7% were other races; and 38% were of Hispanic or Latino ethnicity. Baseline use of stable oral antidepressants was reported in 15% of patients. In Study 2, patients had a mean age of 28 years (range 18 to 44 years); were 56% White, 41% Black or African American, 1% Asian, and 2% were other races; and 23% were of Hispanic or Latino ethnicity. Baseline use of stable oral antidepressants was reported in 19% of patients.

The primary endpoint for Studies 1 and 2 was the change from baseline in depressive symptoms as measured by the HAMD-17 total score at Day 15. In these studies, patients in the ZURZUVAE groups experienced statistically significantly greater improvement on the primary endpoint compared to patients in the placebo groups, as shown in Table 5. For Study 1, the key secondary endpoints included change from baseline in HAMD-17 total score at Days 3, 28, and 45.

Table 5 Results for the Primary Endpoint: Change from Baseline in the HAMD-17 Total Score at Day 15 (Studies 1 and 2 in Women with PPD)
Study Number | Treatment Group | N | Mean Baseline Score (SD) | LS Mean Change from Baseline (SE) | Placebo- subtracted Difference (95% CI)
1 | 50 mg of ZURZUVAE | 98 | 28.6 (2.49) | -15.6 (0.82) | -4.0 (-6.3, -1.7)
1 | Placebo | 97 | 28.8 (2.34) | -11.6 (0.82) | -4.0 (-6.3, -1.7)
2 | Zuranolone (another capsule formulation)* | 76 | 28.4 (2.09) | -17.8 (1.04) | -4.2 (-6.9, -1.5)
2 | Placebo | 74 | 28.8 (2.32) | -13.6 (1.07) | -4.2 (-6.9, -1.5)
HAMD-17: 17-item Hamilton depression rating scale; SD: standard deviation; LS: least squares; SE: standard error; CI: confidence interval
*This capsule formulation of zuranolone is approximately equivalent to 40 mg of ZURZUVAE.

Subgroup analyses of the primary endpoint did not suggest differences in response to 50 mg of ZURZUVAE for age, race, or BMI.

The time course of response for 50 mg ZURZUVAE compared to placebo for Study 1 is shown in Figure 3.

Figure 3 Mean Change from Baseline in HAM-D Total Score Over Time (Days) in Women with PPD in Study 1

*Both phases were double-blind.

14.2 Effects on Driving

Two randomized, double-blind, placebo- and active-controlled, four-way crossover studies (Study 3 and Study 4) evaluated the effects of nighttime ZURZUVAE administration on next-morning driving performance, 9 hours after dosing, using a computer-based driving simulation.

Study 3

In Study 3, 50 mg of ZURZUVAE was administered for six consecutive nights and on the seventh night a single dose of 50 mg or 100 mg (two times the recommended dose) was administered. The primary driving performance outcome measure was the change in Standard Deviation of Lateral Position (SDLP) (a measure of driving impairment) in the ZURZUVAE group compared to the placebo group on Days 2 and 8 (after a single dose and repeat doses, respectively).

Study 3 included 67 healthy participants. The median age was 45 years old (age ranged from 22 to 81 years old; 7 participants were ≥ 65 years of age); there were 38 males and 29 females; 88% were White, 5% were Black or African American, 3% were Asian, and 5% were other races; and 12% were of Hispanic/Latino ethnicity.

A single 50 mg dose of ZURZUVAE caused statistically significant impairment in next-morning driving performance compared to placebo. Statistically significant effects on driving were also observed on Day 8 following daily administration of 50 mg of ZURZUVAE. Administration of 100 mg of ZURZUVAE (twice the maximum recommended dose) on the final night increased impairment in driving ability [see Warnings and Precautions (5.1)].

The exposure-response analysis for driving impairment in Study 3 suggested that the projected mean placebo-adjusted SDLP at 12 hours post-dose would be less than the threshold associated with driving impairment.

Study 4

In Study 4, 30 mg of ZURZUVAE (0.6 times the maximum recommended daily dose) was administered for four consecutive nights and on the fifth night a single dose of 30 mg or 60 mg (1.2 times the recommended daily dose) was administered. The primary driving performance outcome measure was the change in SDLP in the ZURZUVAE group compared to the placebo group on Days 2 and 6 (after a single dose and repeat doses, respectively).

Study 4 included 60 participants; 60% and 40% were male and female, respectively; the median age was 41 years old (range was 22 to 62 years old); 90% were White, 5% were Black or African American, 3% were Asian, and 2% were other races; and 15% were of Hispanic/Latino ethnicity.

A single 30 mg dose of ZURZUVAE caused a statistically significant impairment in next-morning driving performance compared to placebo. The mean effect on driving performance was not statistically significantly different following 30 mg of ZURZUVAE compared to placebo on Day 6; however, driving ability was impaired in some participants taking ZURZUVAE. Administration of 60 mg of ZURZUVAE (1.2 times the maximum recommended dose) on the final night caused statistically significant impairment in next-morning driving performance compared to placebo [see Warnings and Precautions (5.1)].

16 HOW SUPPLIED/STORAGE AND HANDLING

How Supplied

ZURZUVAE (zuranolone) is supplied as 20 mg, 25 mg, and 30 mg capsules as follows:

Capsule Strength | Capsule Colors | Capsule Markings | Packaging Configuration | NDC
20 mg | light-orange cap ivory to light-yellow body | Black “S-217 20 mg” on body | Bottle of 14 | 64406-029-01
25 mg | light-orange cap light-orange body | Black “S-217 25 mg” on body | Bottle of 14 | 64406-030-01
25 mg | light-orange cap light-orange body | Black “S-217 25 mg” on body | Blister pack of 28 | 64406-030-02
30 mg | orange cap light-orange body | Black “S-217 30 mg” on body | Bottle of 14 | 64406-031-01

Storage

Store at room temperature 20°C to 25°C (68°F to 77°F); excursions permitted between 15°C to 30°C (59°F to 86°F) [see USP Controlled Room Temperature].

17 PATIENT COUNSELING INFORMATION

Advise the patient to read the FDA-approved patient labeling (Medication Guide).

Impaired Ability to Drive or Engage in Other Potentially Hazardous Activities

Inform patients that ZURZUVAE causes driving impairment. Advise patients to take ZURZUVAE in the evening. Advise patients not to drive a motor vehicle or engage in other potentially hazardous activities requiring complete mental alertness, such as operating machinery, until at least 12 hours after ZURZUVAE administration. Warn patients that they may not be able to assess their own ability to drive or the degree of impairment caused by ZURZUVAE [see Warnings and Precautions (5.1)].

Central Nervous System Depressant Effects

Inform patients that ZURZUVAE can cause somnolence, dizziness, sedation, and confusion. Advise patients to use caution if taking ZURZUVAE in combination with alcohol, other CNS depressants, or medications that increase the concentration of ZURZUVAE [see Warnings and Precautions (5.2), Adverse Reactions (6.1) and Drug Interactions (7)].

Suicidal Thoughts and Behavior

Advise patients to look for the emergence of suicidal thoughts and behaviors and instruct them to report such symptoms to the healthcare provider immediately [see Warnings and Precautions (5.3)].

Administration Instructions

Inform patients to take ZURZUVAE with fat-containing food [see Dosage and Administration (2.1) and Clinical Pharmacology (12.3)].

Instruct patients that if a daily dose is missed, the missed dose should be taken the next day as scheduled. Patients should be advised not to take extra capsules to make up for the missed dose [see Dosage and Administration (2.1, 2.5)].

Abuse, Misuse, and Physical Dependence

Advise patients that ZURZUVAE has abuse potential with associated risks of misuse, abuse, and substance use disorder including addiction and that ZURZUVAE is associated with the potential for physical dependence [see Drug Abuse and Dependence (9.2, 9.3)].

Pregnancy

Advise pregnant women and females of reproductive potential of the potential risk to a fetus and to notify their healthcare provider if they become pregnant or intend to become pregnant during treatment with ZURZUVAE. Advise female patients of reproductive potential to use effective contraception during treatment with ZURZUVAE and for one week after the final dose [see Warnings and Precautions (5.4), Use in Specific Populations (8.1, 8.3)].

Advise patients that there is a pregnancy exposure registry that monitors pregnancy outcomes in women exposed to ZURZUVAE during pregnancy [see Use in Specific Populations (8.1)].

Manufactured for:
Biogen Inc.
225 Binney Street
Cambridge, MA 02142 USA

ZURZUVAE is a trademark of Sage Therapeutics, Inc.
© 2024 Sage Therapeutics and Biogen

MEDICATION GUIDE
ZURZUVAE™ (zur-ZOO-vay)
(zuranolone)
capsules, for oral use, CIV

What is the most important information I should know about ZURZUVAE?
ZURZUVAE may cause serious side effects, including:

- Decreased ability to drive or do other dangerous activities. ZURZUVAE may decrease your awareness and alertness, which can affect your ability to drive safely or safely do other dangerous activities.
  - Do not drive, operate machinery, or do other dangerous activities until at least 12 hours after taking each dose during your 14-day treatment course of ZURZUVAE.
  - You may not be able to tell on your own if you can drive safely or tell how much ZURZUVAE is affecting you.
- Decreased awareness and alertness [central nervous system (CNS) depressant effects]. ZURZUVAE may cause sleepiness, drowsiness, slow thinking, dizziness, confusion, and trouble walking.
  - Because of these symptoms, you may be at a higher risk for falls during treatment with ZURZUVAE.
  - Taking alcohol, other medicines that cause CNS depressant effects, or opioids while taking ZURZUVAE can make these symptoms worse and may also cause trouble breathing.
  - Tell your healthcare provider if you develop any of these symptoms, or if they get worse during treatment with ZURZUVAE. Your healthcare provider may decrease your dose or stop ZURZUVAE treatment if you develop these symptoms.

What is ZURZUVAE?
ZURZUVAE is a prescription medicine used to treat adults with postpartum depression (PPD).
It is not known if ZURZUVAE is safe and effective for use in children.
ZURZUVAE is a federal controlled substance (C-IV) because it contains zuranolone that can be abused or lead to dependence. Keep ZURZUVAE in a safe place to protect it from theft. Do not sell or give away ZURZUVAE because it may harm others and is against the law.

Before taking ZURZUVAE, tell your healthcare provider about all of your medical conditions, including if you:

- drink alcohol
- have abused or been dependent on prescription medicines, street drugs, or alcohol
- have liver or kidney problems
- are pregnant or plan to become pregnant. ZURZUVAE may harm your unborn baby.
  Females who are able to become pregnant:
  - Tell your healthcare provider right away if you become pregnant or plan to become pregnant during treatment with ZURZUVAE.
  - You should use effective birth control (contraception) during treatment with ZURZUVAE and for 1 week after the final dose.
  - There is a pregnancy registry for females who are exposed to ZURZUVAE during pregnancy. The purpose of the registry is to collect information about the health of females exposed to ZURZUVAE and their baby. If you become pregnant during treatment with ZURZUVAE, talk to your healthcare provider about registering with the National Pregnancy Registry for Antidepressants at 1-844-405-6185 or visit online at https://womensmentalhealth.org/clinical-and-research-programs/pregnancyregistry/antidepressants/
- are breastfeeding or plan to breastfeed. ZURZUVAE passes into breast milk, and it is not known if it can harm your baby. Talk to your healthcare provider about the risks and benefits of breastfeeding and about the best way to feed your baby during treatment with ZURZUVAE.

Tell your healthcare provider about all the medicines you take, including prescription and over-the-counter medicines, vitamins, and herbal supplements.
ZURZUVAE and some medicines may interact with each other and cause serious side effects. ZURZUVAE may affect the way other medicines work and other medicines may affect the way ZURZUVAE works.
Especially tell your healthcare provider if you take:

- antidepressants
- opioids
- CNS depressants such as benzodiazepines

Know the medicines you take. Keep a list of them to show your healthcare provider and pharmacist when you get a new medicine. Your healthcare provider will decide if other medicines can be taken with ZURZUVAE.

How should I take ZURZUVAE?

- Take ZURZUVAE exactly as your healthcare provider tells you to take it.
- Take ZURZUVAE 1 time daily in the evening with fat-containing food for 14 days (a treatment course). Talk to your healthcare provider about examples of foods you should eat.
- If you forget to take ZURZUVAE, skip the missed dose and take the next dose at your regular time the next evening. Do not take extra capsules to make up for the missed dose. Continue taking ZURZUVAE 1 time daily until you complete the rest of your treatment course.
- Your healthcare provider may change your dose of ZURZUVAE if you have certain side effects. Do not change your dose without talking to your healthcare provider.
- If you take too much ZURZUVAE, call your healthcare provider or Poison Help Line at 1-800-222-1222 or go to the nearest hospital emergency room right away.

What should I avoid while taking ZURZUVAE?

- Do not drive a car, operate machinery, or do other dangerous activities until at least 12 hours after taking each dose of ZURZUVAE because ZURZUVAE may make you feel sleepy, confused, or dizzy.
- Do not drink alcohol or take other medicines that make you sleepy or dizzy while taking ZURZUVAE without talking to your healthcare provider.

See “What is the most important information I should know about ZURZUVAE?”

What are the possible side effects of ZURZUVAE?
ZURZUVAE may cause serious side effects, including:

- See “What is the most important information I should know about ZURZUVAE?”
- Increased risk of suicidal thoughts or actions. ZURZUVAE and other antidepressant medicines may increase the risk of suicidal thoughts and actions in people 24 years of age and younger. ZURZUVAE is not for use in children.
  - Depression or other serious mental illnesses are the most important causes of suicidal thoughts or actions.
  How can I watch for and try to prevent suicidal thoughts and actions?
  - Pay close attention to any changes, especially sudden changes in mood, behavior, thoughts, or feelings, or if you develop suicidal thoughts or actions. This is very important when an antidepressant medicine is started or when the dose is changed.
  - Tell your healthcare provider right away if you have any new or sudden changes in mood, behavior, thoughts, or feelings.
  - Keep all follow-up visits with your healthcare provider as scheduled. Call your healthcare provider between visits as needed, especially if you have concerns about symptoms.
  Tell your healthcare provider right away if you have any of the following symptoms, especially if they are new, worse, or worry you:

- attempts to commit suicide
- thoughts about suicide or dying
- new or worse depression
- feeling very agitated or restless
- trouble sleeping (insomnia)
- new or worse anxiety

- panic attacks
- new or worse irritability
- acting aggressive, being angry, or violent
- an extreme increase in activity and talking (mania)
- acting on dangerous impulses
- other unusual changes in behavior or mood

The most common side effects of ZURZUVAE include:

- sleepiness or drowsiness
- dizziness
- common cold

- diarrhea
- feeling tired, weak, or having no energy
- urinary tract infection

These are not all of the possible side effects of ZURZUVAE.
Call your doctor for medical advice about side effects. You may report side effects to FDA at 1-800-FDA-1088.

How should I store ZURZUVAE?

- Store ZURZUVAE at room temperature between 68°F to 77°F (20°C to 25°C).

Keep ZURZUVAE and all medicines out of the reach of children.

General information about the safe and effective use of ZURZUVAE.
Medicines are sometimes prescribed for purposes other than those listed in a Medication Guide. Do not use ZURZUVAE for a condition for which it was not prescribed. Do not give ZURZUVAE to other people, even if they have the same symptoms that you have. It may harm them. You can ask your pharmacist or healthcare provider for information about ZURZUVAE that is written for health professionals.

What are the ingredients in ZURZUVAE?
Active ingredient: zuranolone
Inactive ingredients: ZURZUVAE capsules contain colloidal silicon dioxide, croscarmellose sodium, mannitol, microcrystalline cellulose, and sodium stearyl fumarate. The capsule shells contain gelatin, red iron oxide, titanium dioxide, and yellow iron oxide. The imprinting ink contains ammonium hydroxide, black iron oxide, propylene glycol, and shellac glaze.
Manufactured for:
Biogen Inc., 225 Binney Street, Cambridge, MA 02142
ZURZUVAE is a trademark of Sage Therapeutics, Inc.
For more information about ZURZUVAE go to www.ZURZUVAE.com or call 1-844-987-9882.

This Medication Guide has been approved by the U.S. Food and Drug Administration.

Revised: 07/2024

PACKAGE LABEL

PRINCIPAL DISPLAY PANEL - 30 mg Bottle Carton

NDC 64406-031-01
Rx Only

ZURZUVAE™
CIV
(zuranolone) capsules

30 mg

For oral use

Attention: Dispense
with accompanying
Medication Guide.

14 Capsules

PACKAGE LABEL

PRINCIPAL DISPLAY PANEL - 25 mg Blister Pack Carton

ZURZUVAE™
CIV
(zuranolone) capsules

25 mg per capsule

For oral use

Attention: Dispense
with accompanying
Medication Guide.

28 Capsules

NDC 64406-030-02
Rx Only

Contains a 14-day blister
pack with 28 capsules.

Each capsule contains
25 mg of zuranolone.

50 mg daily dose

21709-4

PACKAGE LABEL

PRINCIPAL DISPLAY PANEL - 20 mg Bottle Carton

NDC 64406-029-01
Rx Only

ZURZUVAE™
CIV
(zuranolone) capsules

20 mg

For oral use

Attention: Dispense
with accompanying
Medication Guide.

14 Capsules